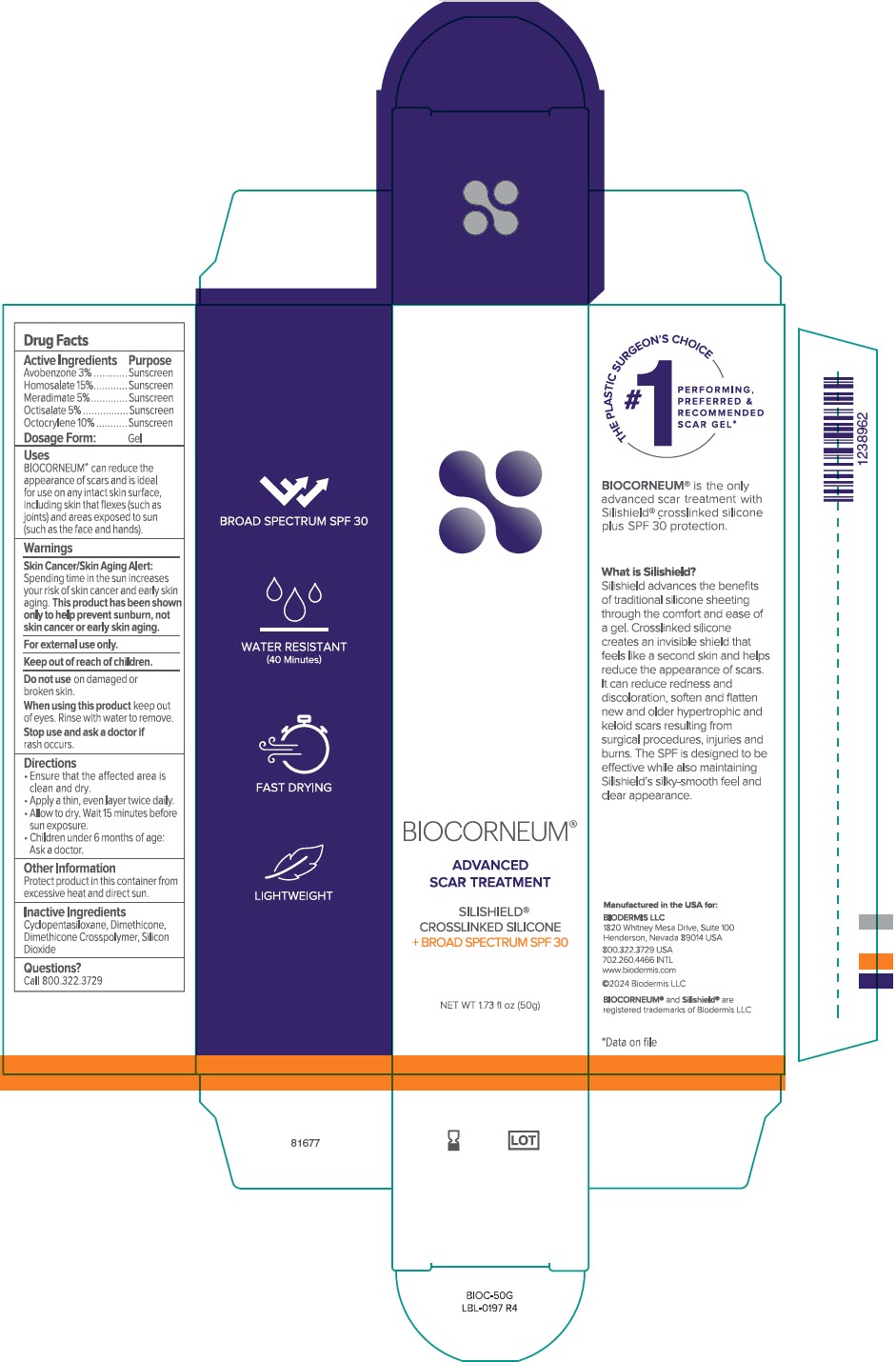 DRUG LABEL: Biocorneum
NDC: 84440-003 | Form: GEL
Manufacturer: Biodermis LLC
Category: otc | Type: HUMAN OTC DRUG LABEL
Date: 20240813

ACTIVE INGREDIENTS: Avobenzone 30 mg/1 g; Homosalate 150 mg/1 g; Meradimate 50 mg/1 g; Octisalate 50 mg/1 g; Octocrylene 100 mg/1 g
INACTIVE INGREDIENTS: CYCLOMETHICONE 5; DIMETHICONE; DIMETHICONE CROSSPOLYMER (450000 MPA.S AT 12% IN CYCLOPENTASILOXANE); SILICON DIOXIDE

Biocorneum®

Drug Facts

ACTIVE INGREDIENT

Active Ingredients | Purpose
Avobenzone 3% | Sunscreen
Homosalate 15% | Sunscreen
Meradimate 5% | Sunscreen
Octisalate 5% | Sunscreen
Octocrylene 10% | Sunscreen

Dosage Form: Gel

Uses

BIOCORNEUM® can reduce the appearance of scars and is ideal for use on any intact skin surface, including skin that flexes (such as joints) and areas exposed to sun (such as the face and hands).

Warnings

Skin Cancer/Skin Aging Alert

Spending time in the sun increases your risk of skin cancer and early skin aging. This product has been shown only to help prevent sunburn, not skin cancer or early skin aging.

For external use only.

Keep out of reach of children.

Do not use on damaged or broken skin.

When using this product keep out of eyes. Rinse with water to remove.

Stop use and ask a doctor if rash occurs.

Directions

- Ensure that the affected area is clean and dry.
- Apply a thin, even layer twice daily.
- Allow to dry. Wait 15 minutes before sun exposure.
- Children under 6 months of age: Ask a doctor.

Other Information

Protect product in this container from excessive heat and direct sun.

Inactive Ingredients

Cyclopentasiloxane, Dimethicone, Dimethicone Crosspolymer, Silicon Dioxide

Questions?

Call 800.322.3729

PRINCIPAL DISPLAY PANEL - 50 g Tube Carton

BIOCORNEUM®

ADVANCED
SCAR TREATMENT

SILISHIELD®
CROSSLINKED SILICONE
+ BROAD SPECTRUM SPF 30

NET WT 1.73 fl oz (50g)